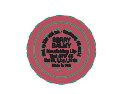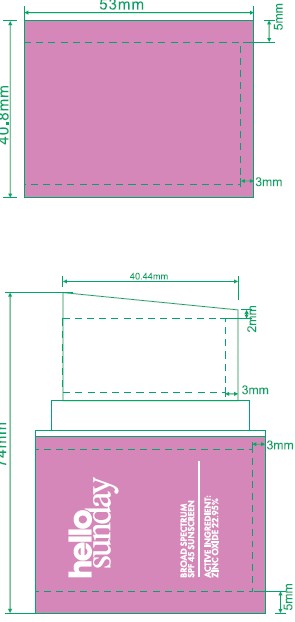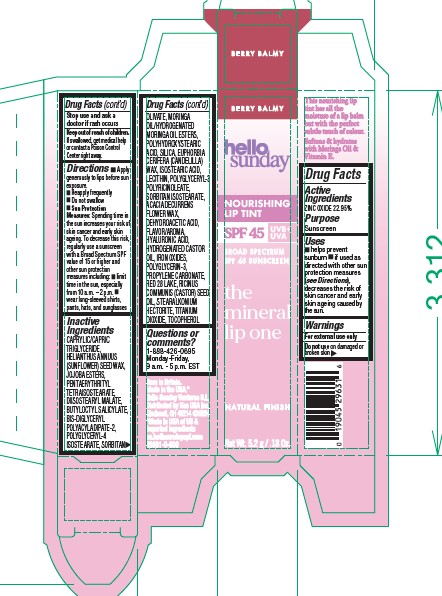 DRUG LABEL: The Mineral Lip One SPF 45 Nourishing Lip Tint Berry Balmy
NDC: 68577-224 | Form: LIPSTICK
Manufacturer: COSMAX USA, CORP
Category: otc | Type: HUMAN OTC DRUG LABEL
Date: 20251231

ACTIVE INGREDIENTS: ZINC OXIDE 22.95 mg/100 mL
INACTIVE INGREDIENTS: HELIANTHUS ANNUUS (SUNFLOWER) SEED WAX; TITANIUM DIOXIDE; ISOSTEARIC ACID; CI 45410; POLYGLYCERYL-3 PENTARICINOLEATE; LECITHIN, SUNFLOWER; EUPHORBIA CERIFERA (CANDELILLA) WAX; BUTYLOCTYL SALICYLATE; DEHYDROACETIC ACID; RICINUS COMMUNIS (CASTOR) SEED OIL; HYDROGENATED CASTOR OIL; CAPRYLIC/CAPRIC TRIGLYCERIDE; POLYGLYCERYL-4 ISOSTEARATE; STEARALKONIUM HECTORITE; TOCOPHEROL; HYALURONIC ACID; CI 77499; SORBITAN ISOSTEARATE; CI 77491; POLYGLYCERIN-3; JOJOBA OIL, RANDOMIZED; PENTAERYTHRITYL TETRAISOSTEARATE; SORBITAN OLIVATE; DIISOSTEARYL MALATE; SILICA; PROPYLENE CARBONATE; CI 77492; ACACIA DECURRENS FLOWER WAX; BIS-DIGLYCERYL POLYACYLADIPATE-2; POLYHYDROXYSTEARIC ACID (2300 MW)

HELLO SUNDAY THE MINERAL LIP ONE NOURISHING LIP TINT SPF 45 BERRY BALMY

Active ingredients

Zinc Oxide 22.95%

Purpose

Sunscreen

USES

- helps prevent sunburn
- if used as directed with other sun protection measures (see Directions), decreases the risk of skin cancer and early skin ageing caused by the sun

Warnings

For external use only

Do not useon damaged or broken skin

Stop use and ask a doctor ifrash occurs

Keep out of reach of children.If swallowed, get medical help or contact a Poison Control Center right away.

DIRECTIONS

- Apply generously to lips before sun exposure.
- Reapply frequently
- Do not swallow
- Sun Protection Measures:Spending time in the sun increases your risk of skin cancer and early skin ageing. To decrease this risk, regularly use a sunscreen with a Broad Spectrum SPF value of 15 or higher and other sun protection measures including:
- limit time in the sun, especially from 10 a.m. - 2 p.m.
- wear long-sleeved shirts, pants, hats, and sunglasses

Inactive Ingredients

Caprylic/Capric Triglyceride, Helianthus Annuus (Sunflower) Seed Wax, Jojoba Esters, Pentaerythrityl Tetraisostearate, Diisostearyl Malate, Butyloctyl Salicylate, Bis-Diglyceryl Polyacyladipate-2, Sorbitan Olivate, Polyglyceryl-4 Isostearate, Moringa Oil/Hydrogenated Moringa Oil Esters, Polyhydroxystearic Acid, Silica, Euphorbia Cerifera (Candelilla) Wax, Isostearic Acid, Lecithin, Polyglyceryl-3 Polyricinoleate, Sorbitan Isostearate, Stearalkonium Hectorite, Flavor, Iron Oxides (Ci 77491), Titanium Dioxide (Ci 77891), Propylene Carbonate, Polyglycerin-3, Acacia Decurrens Flower Wax, Iron Oxides (Ci 77492), Red 28 Lake (Ci 45410), Dehydroacetic Acid, Iron Oxides (Ci 77499), Ricinus Communis (Castor) Seed Oil, Hyaluronic Acid, Hydrogenated Castor Oil, Tocopherol

QUESTIONS OR COMENTS

Questions or comments?

1-888-426-0695. Monday-Friday, 9 a.m. - 5 p.m. EST

PACKAGE LABEL

HELLO SUNDAY THE MINERAL LIP ONE NOURISHING LIP TINT SPF 45 VANILLA CLOUD 5.2g/.18oz